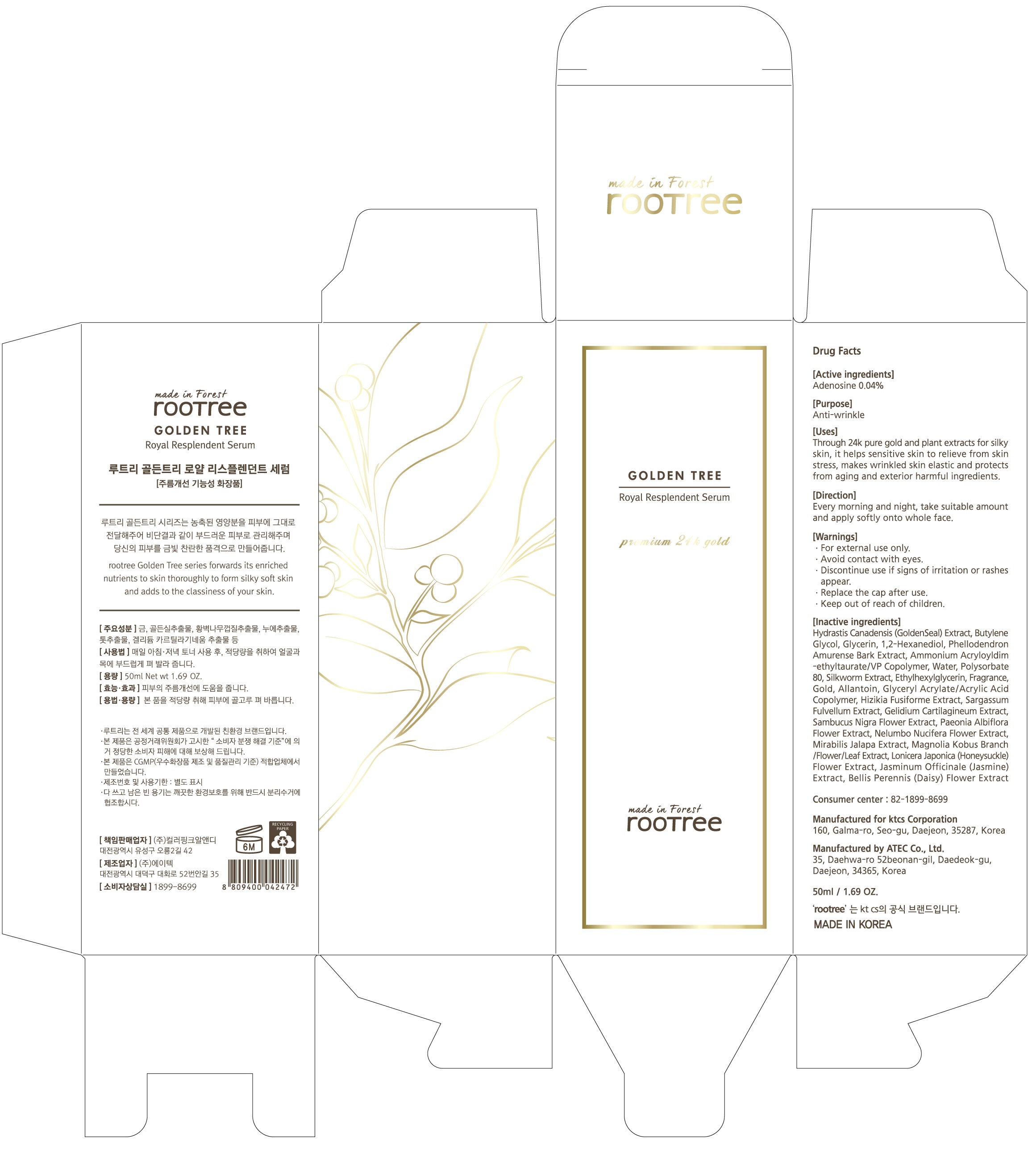 DRUG LABEL: rootree Golden Tree Royal Resplendent Serum
NDC: 72441-120 | Form: LIQUID
Manufacturer: KTCS Corporation
Category: otc | Type: HUMAN OTC DRUG LABEL
Date: 20190624

ACTIVE INGREDIENTS: Adenosine 0.02 g/50 mL
INACTIVE INGREDIENTS: Butylene Glycol; Glycerin

ACTIVE INGREDIENT

Active ingredients: Adenosine 0.04%

INACTIVE INGREDIENT

Inactive ingredients:

Hydrastis Canadensis (GoldenSeal) Extract, Butylene Glycol, Glycerin, 1,2-Hexanediol, Phellodendron Amurense Bark Extract, Ammonium Acryloyldimethyltaurate/VP Copolymer, Water, Polysorbate 80, Silkworm Extract, Ethylhexylglycerin, Fragrance, Gold, Allantoin, Glyceryl Acrylate/Acrylic Acid Copolymer, Hizikia Fusiforme Extract, Sargassum Fulvellum Extract, Gelidium Cartilagineum Extract, Sambucus Nigra Flower Extract, Paeonia Albiflora Flower Extract, Nelumbo Nucifera Flower Extract, Mirabilis Jalapa Extract, Magnolia Kobus Branch/Flower/Leaf Extract, Lonicera Japonica (Honeysuckle) Flower Extract, Jasminum Officinale (Jasmine) Extract, Bellis Perennis (Daisy) Flower Extract

PURPOSE

Purpose: Anti-wrinkle

WARNINGS

For external use only.

Avoid contact with eyes.

Discontinue use if signs of irritation or rashes appear.

Replace the cap after use.

Keep out of reach of children

KEEP OUT OF REACH OF CHILDREN

Uses

Through 24k pure gold and plant extracts for silky skin, it helps sensitive skin to relieve from skin stress, makes wrinkled skin elastic and protects from aging and exterior harmful ingredients.

Directions

Every morning and night, take suitable amount and apply softly onto whole face.